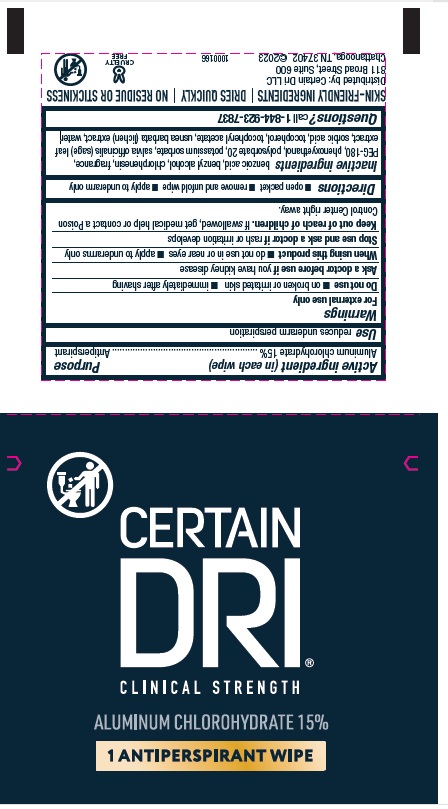 DRUG LABEL: CERTAIN DRI
NDC: 69693-725 | Form: CLOTH
Manufacturer: Clarion Brands, LLC
Category: otc | Type: HUMAN OTC DRUG LABEL
Date: 20251223

ACTIVE INGREDIENTS: ALUMINUM CHLOROHYDRATE 0.15 g/1 g
INACTIVE INGREDIENTS: BENZOIC ACID; BENZYL ALCOHOL; CHLORPHENESIN; POLYETHYLENE GLYCOL 8000; PHENOXYETHANOL; POLYSORBATE 20; POTASSIUM SORBATE; SALVIA OFFICINALIS FLOWERING TOP; SORBIC ACID; TOCOPHEROL; .ALPHA.-TOCOPHEROL ACETATE; USNEA BARBATA; WATER

Drug Facts

Active ingredient (in each wipe) | Purpose
Aluminum chlorohydrate 15% | Antiperspirant

INDICATIONS AND USAGE

Usereduces underarm perspiration

Warnings

For external use only

Do not use

- on broken or irritated skin
- immediately after shaving

Ask a doctor before use ifyou have kidney disease

When using this product

- do not use in or near eyes
- apply to underarms only

Stop use and ask a doctor ifrash or irritation develops

Keep out of reach of children. If swallowed, get medical help or contact a Poison Control Center right away.

Directions

- open packet
- remove and unfold wipe
- apply to underarm only

Inactive ingredients

benzoic acid, benzyl alcohol, chlorphenesin, fragrance, PEG-180, phenoxyethanol, polysorbate 20, potassium sorbate, salvia offcinalis (sage) leaf extract, sorbic acid, tocopherol, tocopheryl acetate, usnea barbata (lichen) extract, water

Questions? c all 1-844-923-7837

PRINCIPAL DISPLAY PANEL

CERTAIN
DRI®
CLINICAL STRENGTH
ALUMINUM CHLOROHYDRATE 15%
1 ANTIPERSPIRANT WIPE
SKIN-FRIENDLY INGREDIENTS | DRIES QUICKLY | NO RESIDUE OR STICKINESS
Distributed by: Certain Dri LLC
811 Broad Street, Suite 600
Chattanooga, TN 37402 ©2023
1000166
CRUELTY
FREE